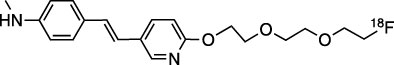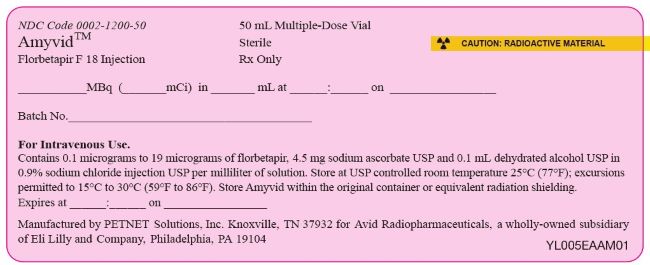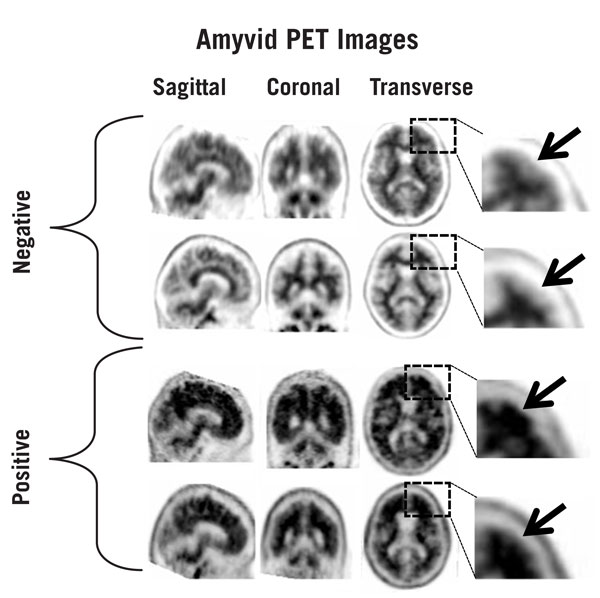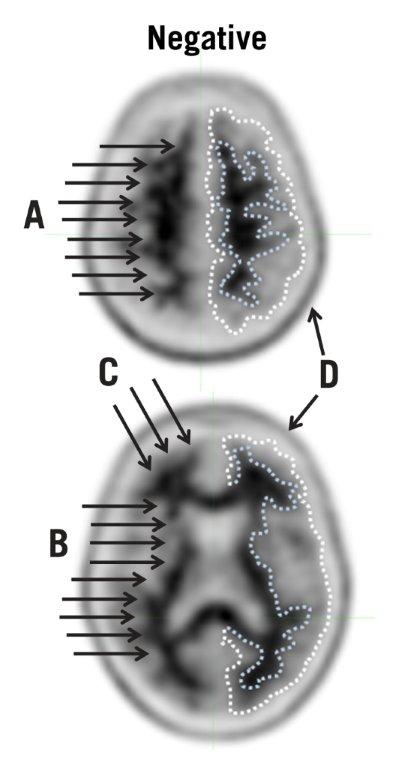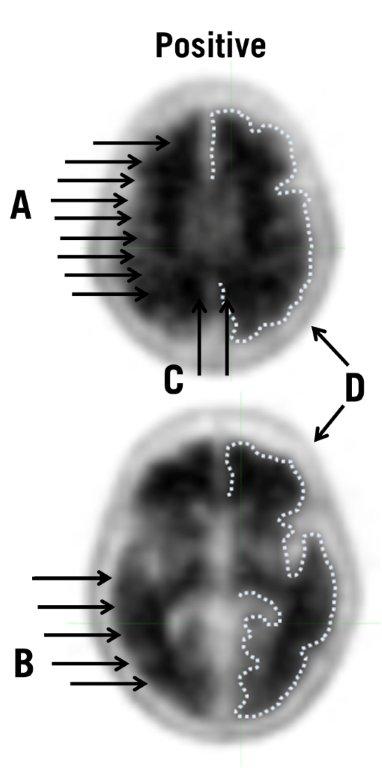 DRUG LABEL: Amyvid
NDC: 0002-1200 | Form: INJECTION, SOLUTION
Manufacturer: Eli Lilly and Company
Category: prescription | Type: HUMAN PRESCRIPTION DRUG LABEL
Date: 20251211

ACTIVE INGREDIENTS: FLORBETAPIR F-18 51 mCi/1 mL
INACTIVE INGREDIENTS: Sodium Ascorbate 4.5 mg/1 mL; Alcohol 78.9 mg/1 mL; Sodium Chloride 8.1 mg/1 mL

HIGHLIGHTS OF PRESCRIBING INFORMATION

These highlights do not include all the information needed to use AMYVID safely and effectively. See full prescribing information for AMYVID.
AMYVID (florbetapir F 18 injection), for intravenous use
Initial U.S. Approval: 2012

RECENT MAJOR CHANGES

Indications and Usage (1) | 6/2025
Dosage and Administration, Image Display and Interpretation (2.4) | 6/2025

1 INDICATIONS AND USAGE

AMYVID is a radioactive diagnostic drug indicated for positron emission tomography (PET) of the brain to estimate amyloid beta neuritic plaque density in adults with cognitive impairment for:

- Evaluation of Alzheimer's disease (AD) and other causes of cognitive decline
- Selection of patients who are indicated for amyloid beta-directed therapy as described in the prescribing information of the therapeutic products (1)

2 DOSAGE AND ADMINISTRATION

- The recommended amount of radioactivity is 370 MBq (10 mCi) administered as a single intravenous bolus in a total volume of up to 10 mL. (2.2)
- Follow the injection with an intravenous flush of approximately 10 mL of 0.9% sodium chloride injection. (2.2)
- Obtain 10-minute PET images starting approximately 30 minutes to 50 minutes after drug administration. (2.3)
- See full prescribing information for image interpretation and radiation dosimetry. (2.4, 2.5)

3 DOSAGE FORMS AND STRENGTHS

Injection: 500 MBq/mL to 1,900 MBq/mL (13.5 mCi/mL to 51 mCi/mL) of florbetapir F 18 in up to 100 mL volume at end of synthesis in a multiple-dose vial (3)

4 CONTRAINDICATIONS

None (4)

5 WARNINGS AND PRECAUTIONS

- Risk of Image Misinterpretation and Other Errors: Image interpretation errors have been observed. (5.1)
- Radiation Risk: AMYVID contributes to a patient's long-term cumulative radiation exposure. Ensure safe drug handling to protect patients and health care providers from unintentional radiation exposure. Advise patients to hydrate before and after administration and to void frequently after administration. (2.1, 2.2, 5.2)

6 ADVERSE REACTIONS

Most common adverse reactions (incidence ≥ 0.4%) were headache, musculoskeletal pain, increased blood pressure, nausea, fatigue, injection site reaction, anxiety, back pain, claustrophobia, dizziness, feeling cold, insomnia, and neck pain. (6.1)

To report SUSPECTED ADVERSE REACTIONS, contact Eli Lilly and Company at 1-800-545-5979 or FDA at 1-800-FDA-1088 or www.fda.gov/medwatch.

8 USE IN SPECIFIC POPULATIONS

Lactation: Temporarily discontinue breastfeeding. A lactating woman should pump and discard breast milk for 24 hours after AMYVID administration. (8.2)

FULL PRESCRIBING INFORMATION

1 INDICATIONS AND USAGE

AMYVID is indicated for positron emission tomography (PET) of the brain to estimate amyloid beta neuritic plaque density in adults with cognitive impairment for:

- Evaluation of Alzheimer's disease (AD) and other causes of cognitive decline
- Selection of patients who are indicated for amyloid beta-directed therapy as described in the prescribing information of the therapeutic products

2 DOSAGE AND ADMINISTRATION

2.1 Radiation Safety - Drug Handling

Handle AMYVID with appropriate safety measures to minimize radiation exposure during administration [see Warnings and Precautions (5.2)]. Use waterproof gloves and effective radiation shielding, including syringe shields when handling and administering AMYVID.

Radiopharmaceuticals, including AMYVID, should be used by or under the control of healthcare providers who are qualified by specific training and experience in the safe use and handling of radionuclides, and whose experience and training have been approved by the appropriate governmental agency authorized to license the use of radionuclides.

2.2 Recommended Dosage and Administration Instructions

Recommended Dosage

The recommended amount of radioactivity of AMYVID is 370 MBq (10 mCi) in a total volume of up to 10 mL, administered as a single intravenous bolus. The maximum mass dose is 50 mcg. Follow the injection with an intravenous flush of approximately 10 mL of 0.9% sodium chloride injection.

Patient Preparation

Instruct patients to hydrate before and after AMYVID administration and to void following AMYVID administration before imaging and frequently thereafter [see Warnings and Precautions (5.2)].

Administration

- Use aseptic technique and radiation shielding when withdrawing and administering AMYVID.
- Visually inspect AMYVID for particulate matter and discoloration prior to administration. Do not use AMYVID if it contains particulate matter or if it is discolored.
- Do not dilute AMYVID.
- Assay the dose in a dose calibrator prior to administration.
- Inject AMYVID through a short intravenous catheter (approximately 1.5 inches or less) to minimize the potential for adsorption of the drug to the catheter. Portions of the AMYVID dose may adhere to longer catheters.
- Dispose of unused product in a safe manner in compliance with applicable regulations.

2.3 Image Acquisition Instructions

- Position the patient supine with the head positioned to center the brain, including the cerebellum, in the PET scanner field of view. Tape or other flexible head restraints may be employed to reduce head movement.
- Acquire 10-minute PET images starting 30 minutes to 50 minutes after AMYVID administration.
- Image reconstruction should include attenuation correction with resulting transaxial pixel sizes between 2 mm and 3 mm.

2.4 Image Display and Interpretation

Image Display

- Display images in the transaxial orientation with access as needed to the sagittal and coronal planes.
- In reviewing the images, include all transaxial slices of the brain using a black-white scale set to the maximum intensity of all the brain pixels.
- Initially locate the brain slice with the highest levels of image contrast (highest signal intensity) and adjust the contrast appropriately.
- Start image interpretation by displaying slices sequentially from the bottom of the brain to the top. Periodically refer to the sagittal and coronal plane image display as needed to better define the signal intensity and to ensure that the entire brain is displayed.

Visual Assessment

AMYVID images should be interpreted only by readers who successfully complete the training program provided by the manufacturer.

Perform image interpretation independently of the patient's clinical features, relying on the recognition of unique image features.

Interpret AMYVID images based upon the distribution of signal intensity within the cerebral cortex by comparing the signal intensity in the cortical gray matter and the adjacent white matter. The signal intensity in the cerebellum does not contribute to the scan interpretation. For example, a positive scan may show retained cerebellar gray-white contrast even when the cortical gray-white contrast is lost.

Some scans may be difficult to interpret due to image noise, atrophy with a thinned cortical ribbon, or image blur. For cases where there is uncertainty as to the location of cortical signal, use co-registered anatomical imaging to improve localization of signal [see Warnings and Precautions (5.1)].

Negative AMYVID Scan

Negative scans show more signal in white matter than in adjacent cortical gray matter, creating clear gray-white contrast.

A negative scan indicates sparse to no amyloid beta neuritic plaques. In patients being evaluated for AD and other causes of cognitive decline who have not been treated with amyloid beta-directed therapy, a negative scan is inconsistent with a neuropathological diagnosis of AD at the time of image acquisition and reduces the likelihood that a patient's cognitive impairment is due to AD. A negative scan result does not preclude the accumulation of amyloid beta in the brain in the future.

Positive AMYVID Scan

Positive scans show cortical areas with reduction or loss of the normally distinct gray-white contrast. These scans will have one or more areas with increased cortical gray matter signal which results in reduced (or absent) gray-white contrast. Specifically, a positive scan will have either:

a) Two or more brain areas (each larger than a single cortical gyrus) in which there is reduced or absent gray-white contrast. This is the most common appearance of a positive scan.
  or
b) One or more areas in which cortical gray matter signal is intense and clearly exceeds the signal in adjacent white matter.

A positive scan establishes the presence of moderate to frequent amyloid beta neuritic plaques. Neuropathological examination has shown that moderate to frequent amyloid beta neuritic plaques are present in patients with AD, but may also be present in patients with other types of neurologic conditions as well as older people with normal cognition.

Figures 1, 2, and 3 provide examples of negative and positive scans.

Figure 1: Examples of AMYVID negative scans (top two rows) and positive scans (bottom two rows). Left to right panels show sagittal, coronal, and transverse PET image slices. Final panel to right shows an enlarged picture of the brain area under the box. The top two arrows are pointing to normal preserved gray-white contrast with cortical signal intensity less than the adjacent white matter. The bottom two arrows indicate areas of decreased gray-white contrast with increased cortical signal intensity that is comparable to the intensity in the adjacent white matter.

Figure 2: Typical Negative Scan. The upper (top) and lower (bottom) transverse slices both show good gray-white matter contrast. The dotted lines illustrate the edge of the cortical gray matter (outer line) and the gray-white border (inner line) and highlight the contrast between less intense signal in the gray matter and more intense signal in the white matter. The arrows illustrate the following points:
A. White matter tracts can be delineated from the frontal lobe to parietal lobe.
B. White matter tracts are clearly identified throughout the occipital / temporal area.
C. Scalloped appearance is seen with “fingers” of white matter in the frontal cortex.
D. Low levels of signal in scalp or skull are distinguished from gray matter signal by the shape and position.

Figure 3: Typical Positive Scan: The upper (top) and lower (bottom) transverse slices show loss of gray-white matter contrast in multiple brain regions. The dotted lines illustrate the edge of the cortical gray matter. Compared to the images from the negative case in Figure 2, the gray matter signal is similar to white matter signal and the gray-white matter border is more difficult to discern. The arrows show the following points:
A. White matter tracts are difficult to fully identify as they travel from frontal to parietal lobe.
B. Borders of white matter tracts in occipital / temporal area are lost in places.
C. Gray matter in medial parietal cortex (precuneus) has increased signal.
D. Low levels of signal in scalp or skull are distinguished from gray matter signal by the shape and position.

Quantitative Analysis

Quantification of amyloid beta neuritic plaque levels (e.g., Centiloid scale or standardized uptake value ratio (SUVR)) can be used in conjunction with visual assessment and performed with FDA-authorized software indicated for quantification of brain amyloid beta PET scans. Refer to the drug manufacturer's training materials for qualitative and quantitative assessment and software manufacturers' documentation for software operation.

2.5 Radiation Dosimetry

Estimated radiation absorbed doses for adults from intravenous injection of AMYVID are shown in Table 1.

Table 1: Estimated Radiation Absorbed Doses in Organs/Tissues in Adults Who Received AMYVID
ORGAN/TISSUE | MEAN ABSORBED DOSE PER UNIT ADMINISTERED ACTIVITY (microGy/MBq)
Adrenal | 14
Brain | 10
Breasts | 6
Gallbladder Wall | 143
Heart Wall | 13
Kidneys | 14
Liver | 64
Lower Large Intestine Wall | 28
Lungs | 9
Muscle | 9
Osteogenic Cells | 28
Ovaries | 18
Pancreas | 14
Red Marrow | 14
Skin | 6
Small Intestine | 66
Spleen | 9
Stomach Wall | 12
Testes | 7
Thymus | 7
Thyroid | 7
Upper Large Intestine Wall | 74
Urinary Bladder Wall | 27
Uterus | 16
Total Body | 12
Effective Dose (microSv/MBq) | 19

The whole-body effective dose resulting from administration of 370 MBq (10 mCi) of AMYVID to an adult is estimated to be 7 mSv. When PET/CT is performed, exposure to radiation will increase by an amount dependent on the settings used in the CT acquisition.

3 DOSAGE FORMS AND STRENGTHS

Injection: 500 MBq/mL to 1,900 MBq/mL (13.5 mCi/mL to 51 mCi/mL) of florbetapir F 18 in up to 100 mL volume at end of synthesis (EOS) as a clear, colorless solution in a multiple-dose vial.

4 CONTRAINDICATIONS

None.

5 WARNINGS AND PRECAUTIONS

5.1 Risk of Image Misinterpretation and Other Errors

Errors may occur in the estimation of brain amyloid beta neuritic plaque density during AMYVID image interpretation [see Clinical Studies (14)].

The use of clinical information in the interpretation of AMYVID images has not been evaluated and may lead to an inaccurate assessment. Extensive brain atrophy as well as motion artifacts that distort the image may limit the ability to distinguish gray and white matter on an AMYVID scan.

Perform image interpretation independently of the patient's clinical information. For cases where there is uncertainty as to the location of cortical signal, use co-registered anatomical imaging to improve localization of signal [see Dosage and Administration (2.4)].

5.2 Radiation Risk

AMYVID contributes to a patient's overall long-term cumulative radiation exposure. Long-term cumulative radiation exposure is associated with an increased risk of cancer. Ensure safe drug handling to protect patients and health care providers from unintentional radiation exposure. Advise patients to hydrate before and after administration and to void frequently after administration [see Dosage and Administration (2.1, 2.2)].

6 ADVERSE REACTIONS

6.1 Clinical Trials Experience

Because clinical trials are conducted under widely varying conditions, adverse reaction rates observed in the clinical trials of a drug cannot be directly compared to rates in the clinical trials of another drug and may not reflect the rates observed in clinical practice.

The safety of AMYVID was evaluated in 555 adult subjects who received AMYVID by intravenous injection in clinical trials. Table 2 shows adverse reactions reported in ≥ 0.4% of subjects from the clinical trials.

Table 2: Adverse Reactions Reported in ≥ 0.4% of Adult Subjects Who Received AMYVID in Clinical Trials
Adverse Reaction | AMYVID N=555 %
Headache | 1.8
Musculoskeletal pain | 0.7
Blood pressure increaseda | 0.7
Nausea | 0.7
Fatigue | 0.5
Injection site reactionb | 0.5
Anxiety | 0.4
Back pain | 0.4
Claustrophobia | 0.4
Dizziness | 0.4
Feeling coldc | 0.4
Insomnia | 0.4
Neck pain | 0.4
a Includes the terms blood pressure increased and hypertension.
b Includes the terms injection site hemorrhage, injection site irritation, and injection site pain.
c Includes the terms feeling cold and chills.

Adverse reactions that occurred in <0.4% of subjects included infusion site rash, dysgeusia, pruritus, urticaria, and flushing.

8 USE IN SPECIFIC POPULATIONS

8.1 Pregnancy

Risk Summary

There are no available data on AMYVID use in pregnant women to evaluate for a drug-associated risk of major birth defects, miscarriage, or adverse maternal or fetal outcomes. Animal reproduction studies have not been conducted with florbetapir F 18 to evaluate its effect on female reproduction and embryo-fetal development.

All radiopharmaceuticals, including AMYVID, have the potential to cause fetal harm depending on the stage of fetal development and the magnitude of the radiation dose. If considering AMYVID administration to a pregnant woman, inform the patient about the potential for adverse pregnancy outcomes based on the radiation dose from the drug and the gestational timing of exposure.

The background risk of major birth defects and miscarriage for the indicated population is unknown. All pregnancies have a background risk of birth defect, loss, or other adverse outcomes. In the U.S. general population, the estimated background risk of major birth defects and miscarriage in clinically recognized pregnancies is 2% to 4% and 15% to 20%, respectively.

8.2 Lactation

Risk Summary

There are no data on the presence of florbetapir F 18 in human milk, the effects on the breastfed infant, or effects on milk production. Lactation studies have not been conducted in animals. Exposure of AMYVID to a breastfed infant can be minimized by temporary discontinuation of breastfeeding (see Clinical Considerations). The developmental and health benefits of breastfeeding should be considered along with the mother's clinical need for AMYVID and any potential adverse effects on the breastfed child from AMYVID or from the underlying maternal condition.

Clinical Considerations

To decrease radiation exposure to the breastfed infant, advise a lactating woman to pump and discard breast milk for 24 hours (>10 half-lives of radioactive decay for the F 18 isotope) following administration of AMYVID.

8.4 Pediatric Use

The safety and effectiveness of AMYVID have not been established in pediatric patients.

8.5 Geriatric Use

Of the 496 patients in clinical studies of AMYVID, 307 patients were 65 years of age and older, while 203 patients were 75 years of age and older. No overall differences in safety or effectiveness were observed between patients 65 years of age and older and younger adult patients.

10 OVERDOSAGE

In the event of administration of a radiation overdose with AMYVID, hydration and frequent urination should be encouraged to minimize radiation exposure to the patient.

11 DESCRIPTION

11.1 Drug Characteristics

AMYVID (florbetapir F 18 injection) is a radioactive diagnostic drug for intravenous use.

Chemically, florbetapir F 18 is (E)-4-(2-(6-(2-(2-(2[^18F] fluoroethoxy)ethoxy)ethoxy)pyridine-3-yl)vinyl)-N-methylbenzamine. The molecular weight is 359 and the structural formula is:

AMYVID is a sterile, non-pyrogenic clear, colorless solution. Each mL contains 0.1 mcg to 19 mcg of florbetapir and 500 MBq to 1,900 MBq (13.5 mCi to 51 mCi) of florbetapir F 18 at EOS and the following inactive ingredients: 4.5 mg sodium ascorbate and 0.1 mL dehydrated alcohol in 0.9% sodium chloride injection. The pH of the solution is between 5.5 and 8.0.

11.2 Nuclear Physical Characteristics

Fluorine-18 (F 18) decays by positron (β^+) emission to oxygen-18 and has a physical half-life of 109.8 minutes. The principal photons useful for diagnostic imaging are the coincident pair of 511 keV gamma photons, resulting from the interaction of the emitted positron with an electron (Table 3).

Table 3: Principal Radiation Produced from Decay of Fluorine-18
Radiation | Energy Level (keV) | Abundance (%)
Positron | 249.8 | 96.9
Gamma | 511 | 193.5

The point source air-kerma coefficient for F 18 is 3.74E -17 Gy m^2/(Bq s); this coefficient was formerly defined as the specific gamma-ray constant of 5.7 R/hr/mCi at 1 cm. The first half-value thickness of lead (Pb) for F 18 gamma rays is approximately 6 mm. The relative reduction of radiation emitted by F 18 that results from various thicknesses of lead shielding is shown in Table 4. The use of ~8 cm of Pb will decrease the radiation transmission (i.e., exposure) by a factor of about 10,000.

Table 4: Radiation Attenuation of 511 keV Gamma Rays by Lead Shielding
Shield Thickness cm of Lead (Pb) | Coefficient of Attenuation
0.6 | 0.5
2 | 0.1
4 | 0.01
6 | 0.001
8 | 0.0001

For use in correcting for physical decay of this radionuclide, the fractions remaining at selected intervals after calibration are shown in Table 5.

Table 5: Physical Decay Chart for Fluorine-18
Minutes | Fraction Remaining
0 | 1.00
15 | 0.909
30 | 0.826
60 | 0.683
110 | 0.500
220 | 0.250
440 | 0.060

12 CLINICAL PHARMACOLOGY

12.1 Mechanism of Action

Florbetapir F 18 binds to amyloid beta plaques and the F 18 isotope produces a positron signal that is detected by a PET scanner. In in vitro binding studies using postmortem human brain homogenates containing amyloid beta plaques, the dissociation constant (Kd) for florbetapir was 3.7 ± 0.3 nM. The binding of florbetapir F 18 to amyloid beta aggregates was demonstrated in postmortem human brain sections using autoradiographic methods, thioflavin S and traditional silver staining correlation studies as well as immunohistochemistry (monoclonal antibody to amyloid beta) correlation studies. Florbetapir binding to tau protein and a battery of neuroreceptors was not detected in in vitro studies.

12.2 Pharmacodynamics

Following intravenous injection, florbetapir F 18 diffuses across the human blood-brain barrier and produces a signal intensity detectable throughout the brain. Subsequently, cerebral perfusion decreases the brain florbetapir F 18 content, with differential retention of the drug in areas that contain amyloid beta aggregates compared to areas that lack the aggregates. The time-activity curves for florbetapir F 18 in the brain of subjects with positive scans show continual signal increases from time zero through 30 minutes post-administration, with stable values thereafter up to at least 90 minutes post-injection. Differences in signal intensity between brain regions showing specific and non-specific florbetapir F 18 uptake form the basis for the image interpretation method [see Dosage and Administration (2.4)].

The test-retest distribution of florbetapir F 18 was evaluated in 21 subjects (11 with probable AD and 10 healthy subjects) who underwent two administrations of florbetapir F 18 (followed by PET scans) separated by a time period of 2 to 30 days. Images were shown to maintain signal distribution reproducibility when evaluated qualitatively (by a reader blinded to image time points) as well as quantitatively using an automated assessment of standardized uptake value ratio (SUVR) in pre-specified brain regions. A comparison of a 10-minute versus a 20-minute image acquisition time showed no difference in the mean cortical to cerebellar SUVR results obtained.

12.3 Pharmacokinetics

Following intravenous administration of 370 MBq (10 mCi) of AMYVID in healthy subjects, florbetapir F 18 was distributed throughout the body with less than 5% of the injected F 18 radioactivity present in the blood by 20 minutes following administration, and less than 2% present by 45 minutes after administration. The F 18 in circulation during the 30-minute to 90-minute imaging window was principally in the form of polar florbetapir metabolites. Whole body scanning following the intravenous injection showed accumulation of radioactivity in the liver within 4 minutes post-injection, followed by elimination of the radioactivity primarily through the biliary/gastrointestinal tract. Some radioactivity is detected in the bladder. Essentially all radioactivity collected in the urine was present as polar metabolites of florbetapir F 18.

Drug Interaction Studies

Clinical

In patients with probable AD, mean cortical SUVR did not differ between patients taking or not taking donepezil, galantamine, or memantine.

In vitro

Effect of acetylcholinesterase inhibitors: donepezil, galantamine, and tacrine did not alter florbetapir F 18 binding to its target.

Effect of amyloid beta-directed therapy: donanemab and lecanemab did not alter florbetapir F 18 binding to its target.

13 NONCLINICAL TOXICOLOGY

13.1 Carcinogenesis, Mutagenesis, Impairment of Fertility

Animal studies to assess the carcinogenicity or reproductive toxicity potential of florbetapir F 18 have not been conducted.

Mutagenesis

In an in vitro bacterial reverse mutation assay (Ames test), increases in the number of revertant colonies were observed in 2 of the 5 strains exposed to ^19F-AV-45, the non-radioactive form of florbetapir F 18. In a chromosomal aberration in vitro study with cultured human peripheral lymphocytes, ^19F-AV-45 did not increase the percentage of cells with structural aberrations with 3-hour exposure with or without activation; however, 22-hour exposure produced a statistically significant increase in structural aberrations at all tested concentrations. Potential in vivo genotoxicity of ^19F-AV-45 was evaluated in a rat micronucleus study. In this assay, ^19F-AV-45 did not increase the number of micronucleated polychromatic erythrocytes at the highest achievable dose level, 372 mcg/kg/day, when given twice daily for 3 consecutive days.

14 CLINICAL STUDIES

14.1 Evaluation of AD and Other Causes of Cognitive Decline

The effectiveness of AMYVID was evaluated in two single-arm clinical studies (i.e., Studies 1 and 2) in subjects with a range of cognitive function, including some terminally ill subjects who had agreed to participate in a postmortem brain donation program as well as healthy subjects. Subjects underwent an AMYVID injection and scan. The images were interpreted using a clinically applicable binary image interpretation method (negative or positive) by five independent readers who were blinded to all clinical information [see Dosage and Administration (2.3, 2.4)]. Image interpretations used co-registration with CT scans when PET scans were performed on dual PET-CT scanners. Before image interpretation, all readers underwent special training on image interpretation: in-person training or electronic media training.

The neuritic plaque density in both studies was determined using an algorithm in which microscopic measures of highest plaque density within a brain region were averaged to produce an estimate of global neuritic plaque density. The global neuritic plaque density was categorized in the same manner as that for a region (Table 6), where plaques were counted on slides with modified Bielschowsky silver stained tissue sections. To determine the agreement between the in vivo AMYVID image results and the postmortem amyloid beta neuritic plaque density, AMYVID results (negative or positive) were pre-specified to correspond to specific histopathology-derived plaque density scores, based upon a modification of the Consortium to Establish a Registry for Alzheimer's Disease (CERAD) criteria, which use neuritic plaque counts as a necessary pathological feature of AD.

Table 6: Categorization of Histopathology and AMYVID PET Read
Histopathology Categorization |  | AMYVID PET Read
Neuritic Plaque Counts | CERAD Score | AMYVID PET Read
<1 | none | Negative
1 - 5 | sparse | Negative
6 - 19 | moderate | Positive
20+ | frequent | Positive

Study 1 evaluated performance characteristics (sensitivity and specificity) in terminally ill subjects by comparing premortem AMYVID scans to a postmortem truth standard of amyloid beta neuritic plaque density. A total of 59 subjects underwent autopsy after being dosed with AMYVID and imaged. The mean age was 79 years (range 47 to 103 years), half were females, and most were White (93%). A total of 29 subjects had an AD clinical diagnosis, 13 had another type of dementing disorder, 5 had mild cognitive impairment (MCI), and 12 had no cognitive impairment. The time interval between the AMYVID scan and death was less than one year for 46 subjects and between one and two years for 13 subjects. At autopsy, the global brain neuritic plaque density category (CERAD score as in Table 6) was: frequent (n=30); moderate (n=9); sparse (n=5); and none (n=15).

Study 2 evaluated inter-reader and intra-reader reproducibility of image interpretation using images from 59 subjects with a truth standard (same subjects as in Study 1) and 92 subjects without a truth standard (52 subjects with MCI, 20 subjects with AD, and 20 healthy subjects). Intra-reader reproducibility was assessed with images from 33 subjects (22%). Among the 151 subjects, the mean age was 75 years (range 47 to 103 years), half were females, and most were White (93%).

Among all subjects who underwent autopsy within two years (n=59; 39 positive and 20 negative based on histopathology), the sensitivity using the majority interpretation of the readers trained in-person (Study 1) was 92% (95% CI: 78%, 98%) and specificity was 100% (95% CI: 80%, 100%). The median (and range) of correct, false negative, and false positive reads were 55 (45, 56), 3 (2, 12), 1 (0, 2), respectively, for in-person training; and were 51 (46 to 54), 7 (3 to 12), 1 (1 to 2), respectively, for electronic media training. Table 7 shows the inter-reader reproducibility results among readers who underwent electronic media training (Study 2) for various groups of subjects. Inter-reader reproducibility analyses for all images showed an overall Fleiss' kappa statistic of 0.83 (95% CI: 0.78, 0.88); the lower bound of the 95% CI exceeded the pre-specified success criterion of 0.58. Intra-reader reproducibility analyses showed that between the two readings for each of the 33 duplicate scans, one of the five readers had complete agreement for all 33 scans, two readers had discrepant reads for a single scan, one reader had discrepant reads for two scans, and another reader had discrepant reads for three scans.

Table 7: Inter-Reader Reproducibility of AMYVID PET Read Results for Various Subject Groups in Study 2a
Subject Group by Cognitive Status and Truth Standard (TS) | Positive Scans, nb | Kappa (95% CI) | Percent of Scans with Inter-Reader Agreement
Subject Group by Cognitive Status and Truth Standard (TS) | Positive Scans, nb | Kappa (95% CI) | 3 of 5 readers agreed | 4 of 5 readers agreed | 5 of 5 readers agreed
All subjects with a TS, n=59 | 33 | 0.75 (0.67, 0.83) | 14 | 10 | 76
All subjects without a TS, n=92 | 33 | 0.88 (0.82, 0.94) | 2 | 11 | 87
AD, n=49 (29 with TS; 20 no TS) | 38 | 0.67 (0.58, 0.76) | 10 | 14 | 76
MCI, n=57 (5 with TS; 52 no TS) | 17 | 0.91 (0.83, 0.99) | 2 | 7 | 91
Other non-AD dementia with TS, n=13 | 7 | 0.52 (0.35, 0.69) | 23 | 23 | 54
Cognitively normal with TS, n=12 | 1 | 0.73 (0.55, 0.87) | 0 | 8 | 92
Healthy subjects without TS, n=20 | 4 | 0.83 (0.69, 0.97) | 5 | 5 | 90
a Readers who underwent electronic media training.
b Shown is the median number of scans interpreted as positive across the five readers for each subgroup of subjects listed in the first column.

14.2 Selection of Patients Indicated for Amyloid Beta-Directed Therapy

Refer to the Prescribing Information of amyloid beta-directed therapy for description of clinical trials in which the efficacy of amyloid beta PET for selecting patients has been established.

Brain amyloid beta PET scans have been used to assess reduction of plaque in some clinical trials of amyloid beta-directed therapies as also described in the prescribing information of the therapeutic products.

16 HOW SUPPLIED/STORAGE AND HANDLING

How Supplied

AMYVID (florbetapir F 18 injection) is a clear, colorless solution supplied in a shielded multiple-dose vial available as:

Concentration @ EOS | Volume | Vial Size | NDC
500 MBq/mL to 1,900 MBq/mL (13.5 mCi/mL to 51 mCi/mL) | 10 mL to 50 mL | 50 mL | 0002-1200-50
500 MBq/mL to 1,900 MBq/mL (13.5 mCi/mL to 51 mCi/mL) | 10 mL to 100 mL | 100 mL | 0002-1200-48

Storage and Handling

Store AMYVID in the original container with radiation shielding at 25ºC (77°F); excursions permitted to 15ºC to 30ºC (59°F to 86°F) [see USP Controlled Room Temperature].

AMYVID does not contain a preservative.

Do not use after the expiration date and time provided on the container label.

AMYVID multiple-dose vial expires 10 hours after EOS.

Dispose of unused product in accordance with all federal, state, and local laws and institutional requirements.

This preparation is for use by persons under license by the Nuclear Regulatory Commission or the relevant regulatory authority of an Agreement State.

17 PATIENT COUNSELING INFORMATION

Radiation Risk

Advise patients of the radiation risk of AMYVID. Instruct patients to drink water to ensure adequate hydration prior to administration of AMYVID and to continue drinking and voiding frequently following administration to reduce radiation exposure [see Warnings and Precautions (5.2)].

Pregnancy

Inform pregnant women of the potential risks of fetal exposure to radiation doses with AMYVID [see Use in Specific Populations (8.1)].

Lactation

Advise a lactating woman to temporarily discontinue breastfeeding and to pump and discard breast milk for 24 hours (>10 half-lives of radioactive decay for the F 18 isotope) after AMYVID administration to minimize radiation exposure to the breastfed infant [see Use in Specific Populations (8.2)].

Marketed by
Lilly USA, LLC
Indianapolis, IN 46285
USA

Copyright © 2012, 2025, Eli Lilly and Company. All rights reserved.

AMV-0005-USPI-20250709

PACKAGE LABEL – Amyvid 50 mL PETNET Label

NDC Code 0002-1200-50
50 mL Multiple-Dose Vial
Sterile
Rx only

☢ CAUTION: RADIOACTIVE MATERIAL

AmyvidTM

Florbetapir F 18 Injection

____MBq (____mCi) in ____mL at ____:____ on ____

Batch No. ________________

For Intravenous Use.

Contains 0.1 to 19 micrograms of florbetapir, 4.5 mg sodium ascorbate USP and 0.1 mL dehydrated alcohol USP in 0.9% sodium chloride injection USP per milliliter of solution. Store at USP controlled room temperature 25ºC (77ºF); excursions permitted to 15ºC to 30ºC (59ºF to 86ºF). Stopre Amyvid within the original container or eqivalent radiation shielding.

Expires at ____:____ on ______________

Manufactured by PETNET Solutions, Inc. Knoxville, TN 37932 for Avid Radiopharmaceuticals, a wholly-owned subsidiary of Eli Lilly and Company, Philadelphia, PA 19104